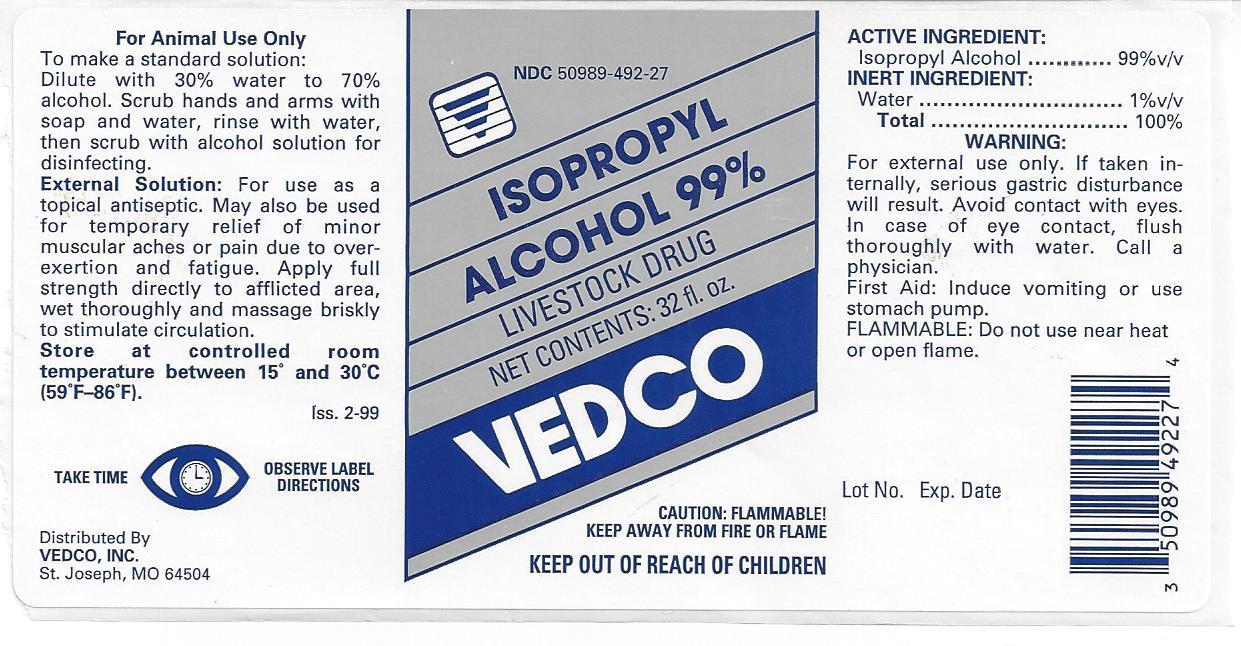 DRUG LABEL: Isopropyl Alcohol
NDC: 50989-492 | Form: LIQUID
Manufacturer: Vedco
Category: animal | Type: OTC ANIMAL DRUG LABEL
Date: 20130923

ACTIVE INGREDIENTS: ISOPROPYL ALCOHOL 99 mL/100 mL
INACTIVE INGREDIENTS: WATER

Isopropyl Alcohol 99%

NDC 50989-492-27 ISOPROPYL ALCOHOL 99% LIVESTOCK DRUG NET CONTENTS: 32 fl. oz.

VEDCO

CAUTION: FLAMMABLE!

KEEP AWAY FROM FIRE OR FLAME

KEEP OUT OF REACH OF CHILDREN

For Animal Use Only

To make a standard solution:

Dilute with 30% water to 70% alcohol. Scrub hands and arms with soap and water, rinse with water, then scrub with alcohol solution for disinfecting.

External Solution: For use as a topical antispectic. May also be used for temporary relief of minor muscular aches or pain due to overexertion and fatigue. Apply full strength directly to afflicted area, wet thoroughy and massage briskly to stimulate circulation.

Store at controlled room temperature between 15° and 30°C (59°F-86°F).

TAKE TIME OBSERVE LABEL DIRECTIONS

Distributed By

VEDCO, INC.

St. Joseph, MO 64504

ACTIVE INGREDIENT:

Isopropyl Alcohol..............99%v/v

INERT INGREDIENT:

WATER……………………………………….1% v/v

TOTAL………………………………………..100%

WARNING:

For external use only. If taken internally, serious gastric disturbance will result. Avoid contact with eyes. In case of eye contact, flush thoroughly with water. Call a physician.

First Aid: Induce vomiting or use stomach pump.

FLAMMABLE: Do not use near heat or open flame.

Lot No. Exp. Date

IPA Bottle Label